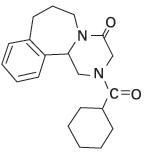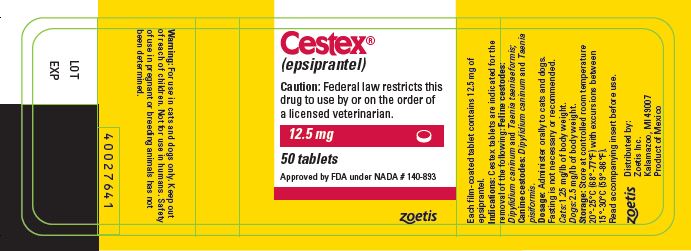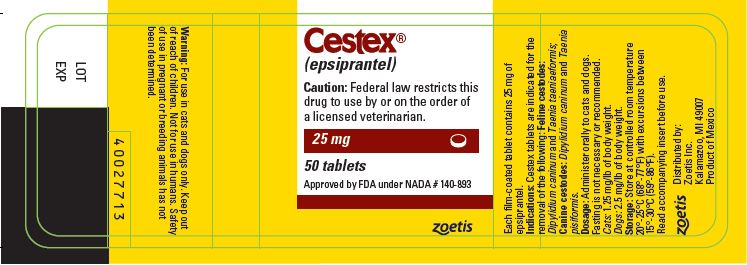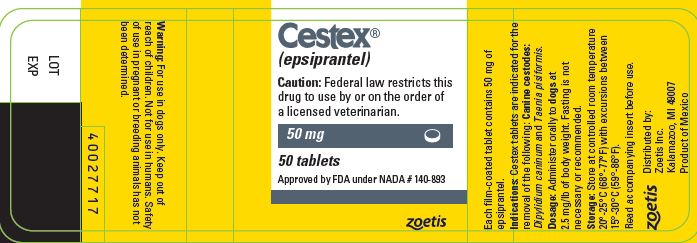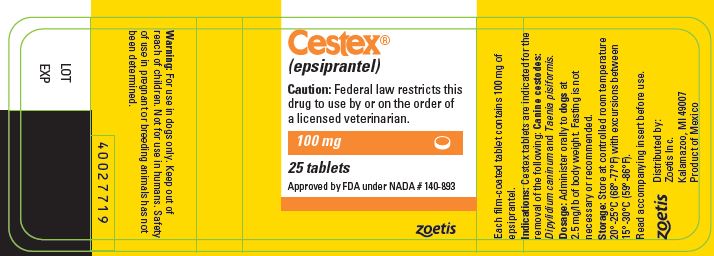 DRUG LABEL: Cestex
NDC: 54771-8032 | Form: TABLET, FILM COATED
Manufacturer: Zoetis Inc.
Category: animal | Type: PRESCRIPTION ANIMAL DRUG LABEL
Date: 20191002

ACTIVE INGREDIENTS: epsiprantel 12.5 mg/1 1

Cestex®
(epsiprantel)

Veterinary Tablets

Cestex (epsiprantel) tablets are indicated for the removal of tapeworms in the cat (Dipylidium caninum and Taenia taeniaeformis) and dog (Dipylidium caninum and Taenia pisiformis).

CAUTION

Federal law restricts this drug to use by or on the order of a licensed veterinarian.

DESCRIPTION

Cestex tablets are film-coated and contain 12.5 mg, 25 mg, 50 mg or 100 mg of epsiprantel per tablet.

Epsiprantel is an anthelmintic that is active as a single dose against the common tapeworms of cats and dogs. Epsiprantel has a molecular weight of 326 and is chemically 2-(cyclohexyl-carbonyl)-4-oxo 1,2,3,4,6,7,8,12b-octahydropyrazino[2,1-a][2]benza-zepine. It is a stable white solid which is sparingly soluble in water. Its chemical structure is presented below.

Action

Epsiprantel acts directly on the tapeworm. Since it is minimally absorbed following oral administration, epsiprantel remains at the site of action within the gastrointestinal tract. Due to digestive process, tapeworm fragments or proglottids may not be readily visible in the stool.

INDICATIONS AND USAGE

Cestex tablets are indicated for the removal of the following:

Feline cestodes: Dipylidium caninum and Taenia taeniaeformis

Canine cestodes: Dipylidium caninum and Taenia pisiformis

CONTRAINDICATIONS

There are no known contraindications to the use of this drug.

WARNINGS

For use in cats and dogs only. Safety of use in pregnant or breeding animals has not been determined. Keep out of reach of children. Not for use in humans.

PRECAUTION

Do not use in kittens or puppies less than 7 weeks of age.

DOSAGE AND ADMINISTRATION

Cestex tablets should be administered orally.

The recommended dosage of epsiprantel is: cats, 1.25 mg/lb of body weight; dogs, 2.5 mg/lb of body weight. The following table may be used as a guide:

Dosage Schedule
Feline
Body Weight | Dose
Seven weeks old up to 10 lb | 12.5 mg
11–20 lb | 25.0 mg
Canine
Body Weight | Dose
Seven weeks old up to 5 lb | 12.5 mg
6–10 lb | 25.0 mg
11–20 lb | 50.0 mg
21–40 lb | 100.0 mg
41–50 lb | 125.0 mg
51–60 lb | 150.0 mg
61–80 lb | 200.0 mg
81–90 lb | 225.0 mg
91–100 lb | 250.0 mg
101+ lb | 2.5 mg/lb, rounding up to next whole tablet combination

Fasting is not necessary or recommended.

Unless exposure to the infected intermediate hosts is controlled, reinfection is likely and retreatment may be required. In the case of D. caninum, an effective flea control program should be instituted.

SAFETY

Epsiprantel has been evaluated in cats at 5 times the recommended dose given once daily for 3 days with no adverse effects noted. In tolerance studies, epsiprantel produced minimal clinical signs in cats given 40 times the recommended dose once daily for 4 days.

Epsiprantel has been evaluated in 14-day repeat dose studies in dogs at 500 mg/kg (90 times recommended dosage) with no significant adverse results. No side effects were observed during the clinical field studies.

Epsiprantel is not a cholinesterase inhibitor. During the course of clinical field studies, Cestex was administered concurrently with diethylcarbamazine citrate (dogs only), anti-inflammatory agents, insecticides, and nematocides with no drug incompatibilities noted.

STORAGE

Store at controlled room temperature 20°-25°C (68°-77°F) with excursions between 15°-30°C (59°-86°F).

HOW SUPPLIED

Cestex tablets are film-coated and contain 12.5 mg, 25 mg, 50 mg or 100 mg of epsiprantel per tablet. Cestex is supplied as described below:

 | Weight (lbs) |  | Number
Concentration | Cat | Dog | Tablets/Bottle
12.5 mg | 10 | 5 | 50, 100
25.0 mg | 20 | 10 | 50, 100
50.0 mg | – – | 20 | 25, 50
100.0 mg | – – | 40 | 25, 50

Approved by FDA under NADA # 140-893

zoetis

Distributed by:
Zoetis Inc.
Kalamazoo, MI 49007

40027642

Revised: May 2019

PRINCIPAL DISPLAY PANEL - 12.5 mg Bottle Label

Cestex®
(epsiprantel)

Caution: Federal law restricts this drug to use by or on the order of a licensed veterinarian.

12.5 mg

50 tablets

Approved by FDA under NADA # 140-893

zoetis